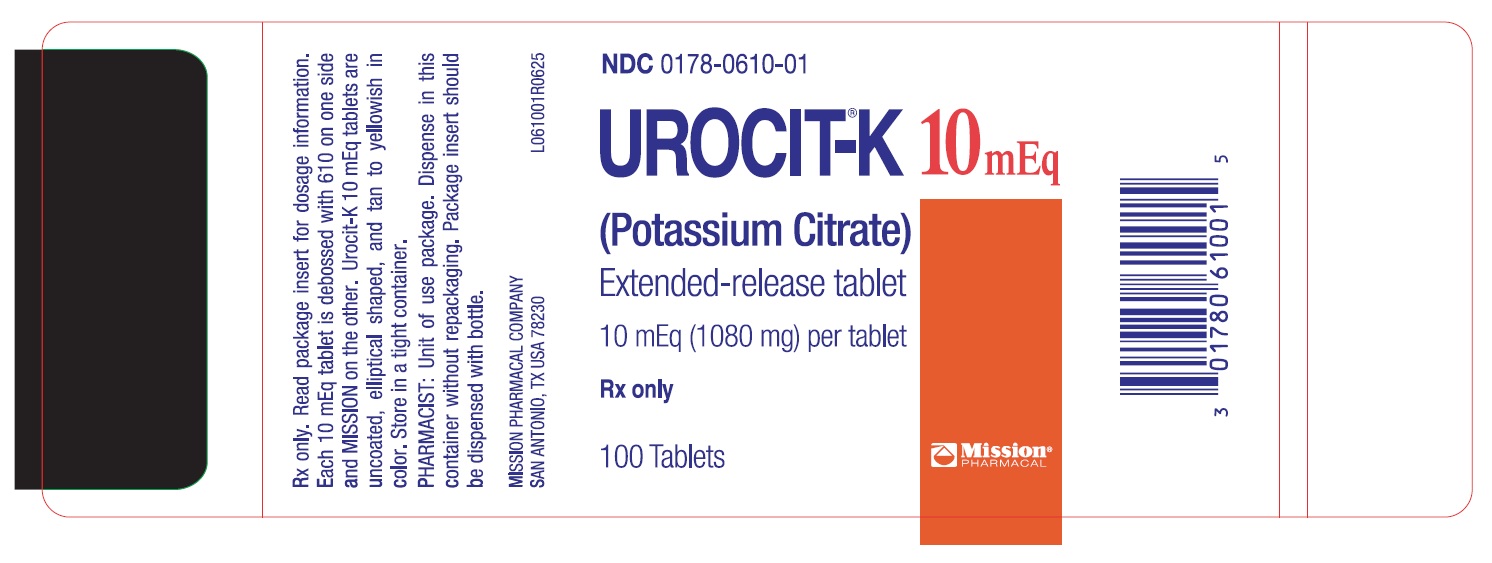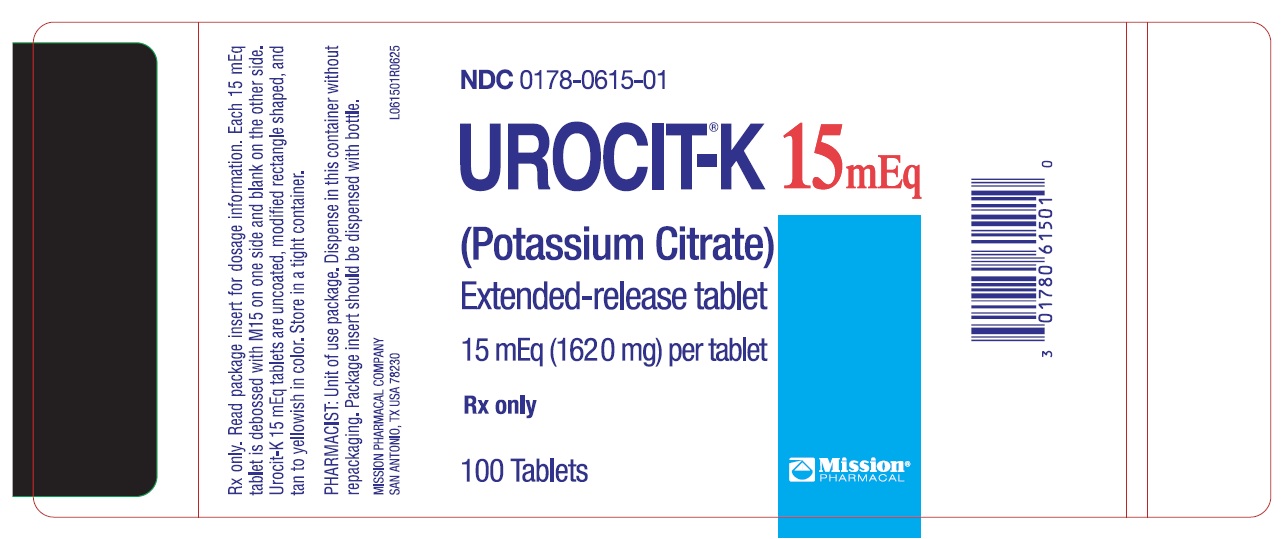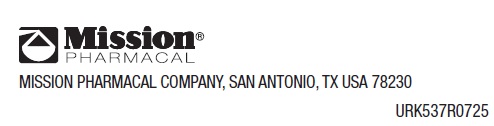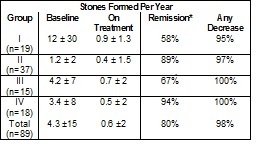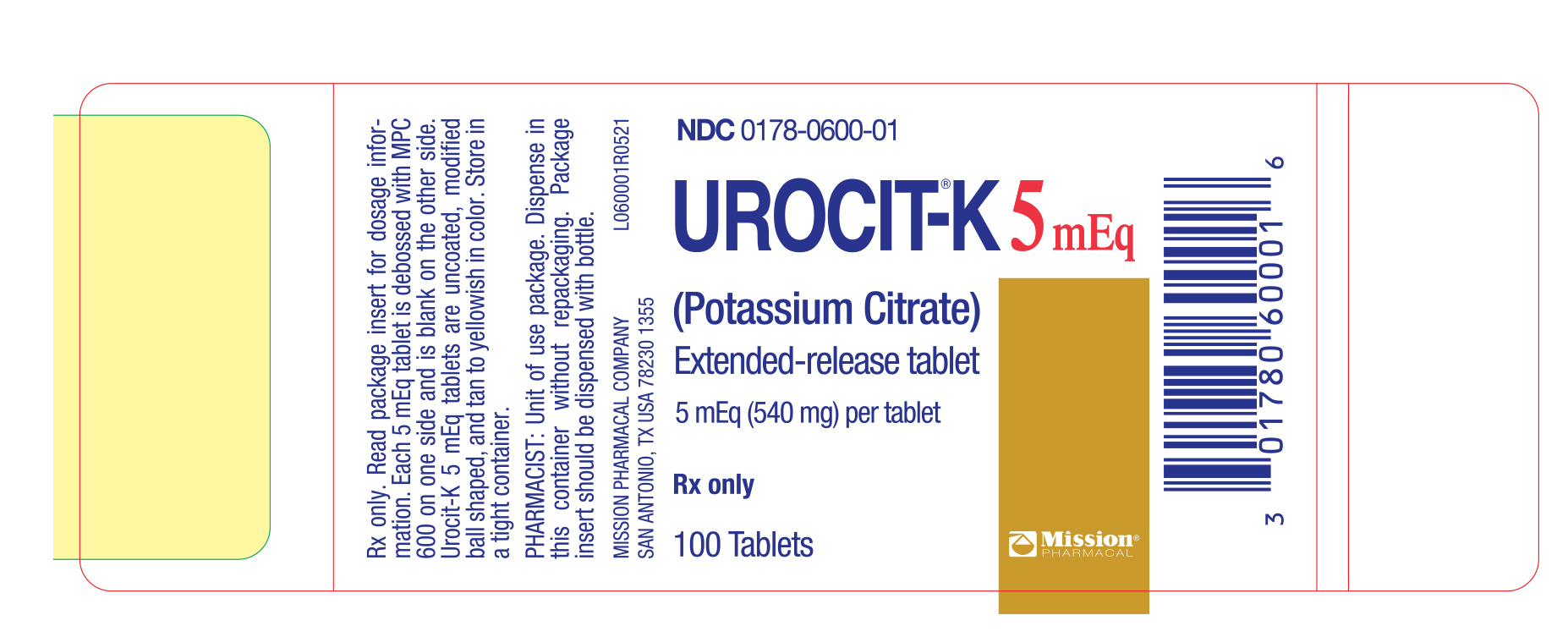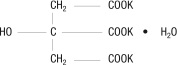 DRUG LABEL: UROCIT-K
NDC: 0178-0610 | Form: TABLET, EXTENDED RELEASE
Manufacturer: Mission Pharmacal Company
Category: prescription | Type: HUMAN PRESCRIPTION DRUG LABEL
Date: 20251202

ACTIVE INGREDIENTS: POTASSIUM CITRATE 10 meq/1 1
INACTIVE INGREDIENTS: MAGNESIUM STEARATE; CARNAUBA WAX

HIGHLIGHTS OF PRESCRIBING INFORMATION

Urocit ®-K (Potassium Citrate) Extended Release Tablets for Oral Use
These highlights do not include all the information needed to use Urocit®-K safely and effectively. See full prescribing information for Urocit®-K.
Initial U.S. Approval: 1985

1 INDICATIONS AND USAGE

Urocit-K is a citrate salt of potassium indicated for the management of:

- Renal tubular acidosis (RTA) with calcium stones (1.1)
- Hypocitraturic calcium oxalate nephrolithiasis of any etiology (1.2)

- Uric acid lithiasis with or without calcium stones (1.3)

2 DOSAGE AND ADMINISTRATION

Objective: To restore normal urinary citrate (greater than 320 mg/day and as close to the normal mean of 640 mg/day as possible), and to increase urinary pH to a level of 6.0 to 7.0.

- Severe hypocitraturia (urinary citrate < 150 mg/day): therapy should be initiated at 60 mEq per day; a dose of 30 mEq two times per day or 20 mEq three times per day with meals or within 30 minutes after meals or bedtime snack (2.2)

- Mild to moderate hypocitraturia (urinary citrate >150 mg/day): therapy should be initiated at 30 mEq per day; a dose of 15 mEq two times per day or 10 mEq three times per day with meals or within 30 minutes after meals or bedtime snack (2.3)

3 DOSAGE FORMS AND STRENGTHS

Tablets: 10 mEq and 15 mEq (3)

4 CONTRAINDICATIONS

- Patients with hyperkalemia (or who have conditions predisposing them to hyperkalemia). Such conditions include chronic renal failure, uncontrolled diabetes mellitus, acute dehydration, strenuous physical exercise in unconditioned individuals, adrenal insufficiency, extensive tissue breakdown (4)
- Patients for whom there is cause for arrest or delay in tablet passage through the gastrointestinal tract such as those suffering from delayed gastric emptying, esophageal compression, intestinal obstruction or stricture (4)
- Patients with peptic ulcer disease (4)
- Patients with active urinary tract infection (4)
- Patients with renal insufficiency (glomerular filtration rate of less than 0.7 ml/kg/min) (4)

5 WARNINGS AND PRECAUTIONS

- Hyperkalemia: In patients with impaired mechanisms for excreting potassium, Urocit-K administration can produce hyperkalemia and cardiac arrest. Potentially fatal hyperkalemia can develop rapidly and be asymptomatic. The use of Urocit-K in patients with chronic renal failure, or any other condition which impairs potassium excretion such as severe myocardial damage or heart failure, should be avoided (5.1)
- Gastrointestinal lesions: if there is severe vomiting, abdominal pain or gastrointestinal bleeding, Urocit-K should be discontinued immediately and the possibility of bowel perforation or obstruction investigated (5.2)

6 ADVERSE REACTIONS

Some patients may develop minor gastrointestinal complaints such as abdominal discomfort, vomiting, diarrhea, loose bowel movements or nausea. These may be alleviated by taking the dose with meals or snacks or by reducing the dosage (6.1)

To report SUSPECTED ADVERSE REACTIONS, contact Mission Pharmacal Company at 1-800-298-1087 or FDA at 1-800-FDA-1088 or www.fda.gov/medwatch.

7 DRUG INTERACTIONS

The following drug interactions may occur with potassium citrate:

- Potassium-sparing diuretics: concomitant administration should be avoided since the simultaneous administration of these agents can produce severe hyperkalemia (7.1)
- Drugs that slow gastrointestinal transit time: These agents (such as anticholinergics) can be expected to increase the gastrointestinal irritation produced by potassium salts (7.2)
- Renin-angiotensin-aldosterone inhibitors: Monitor for hyperkalemia (7.3)
- Nonsteroidal Anti-inflammatory drugs (NSAIDs) monitor for hyperkalemia (7.4)

8 USE IN SPECIFIC POPULATIONS

- Pregnant women: Animal reproduction studies have not been conducted. It is not known whether Urocit-K can cause fetal harm when administered to a pregnant woman or can affect reproduction capacity. Urocit-K should be given to a pregnant woman only if clearly needed (8.1)
- Nursing mothers: The normal potassium ion content of human milk is about 13 mEq/L. It is not known if Urocit-K has an effect on this content. Urocit-K should be given to a woman who is breastfeeding only if clearly needed (8.3)
- Pediatric Use: Safety and effectiveness in children have not been established (8.4)

See 17 for PATIENT COUNSELING INFORMATION

Revised 12/2021

FULL PRESCRIBING INFORMATION

1 INDICATIONS AND USAGE

1.1 Renal Tubular Acidosis (RTA) with Calcium Stones

Potassium citrate is indicated for the management of renal tubular acidosis [see Clinical Studies (14.1)].

1.2 Hypocitraturic Calcium Oxalate Nephrolithiasis of any Etiology

Potassium citrate is indicated for the management of Hypocitraturic calcium oxalate nephrolithiasis [see Clinical Studies (14.2)].

1.3 Uric Acid Lithiasis with or without Calcium Stones

Potassium citrate is indicated for the management of Uric acid lithiasis with or without calcium stones [see Clinical Studies (14.3)].

2 DOSAGE AND ADMINISTRATION

2.1 Dosing Instructions

Treatment with extended release potassium citrate should be added to a regimen that limits salt intake (avoidance of foods with high salt content and of added salt at the table) and encourages high fluid intake (urine volume should be at least two liters per day). The objective of treatment with Urocit-K is to provide Urocit-K in sufficient dosage to restore normal urinary citrate (greater than 320 mg/day and as close to the normal mean of 640 mg/day as possible), and to increase urinary pH to a level of 6.0 or 7.0.

Monitor serum electrolytes (sodium, potassium, chloride and carbon dioxide), serum creatinine and complete blood counts every four months and more frequently in patients with cardiac disease, renal disease or acidosis. Perform electrocardiograms periodically. Treatment should be discontinued if there is hyperkalemia, a significant rise in serum creatinine or a significant fall in blood hematocrit or hemoglobin.

2.2 Severe Hypocitraturia

In patients with severe hypocitraturia (urinary citrate < 150 mg/day), therapy should be initiated at a dosage of 60 mEq/day (30 mEq two times/day or 20 mEq three times/day with meals or within 30 minutes after meals or bedtime snack). Twenty-four hour urinary citrate and/or urinary pH measurements should be used to determine the adequacy of the initial dosage and to evaluate the effectiveness of any dosage change. In addition, urinary citrate and/or pH should be measured every four months. Doses of Urocit-K greater than 100 mEq/day have not been studied and should be avoided.

2.3 Mild to Moderate Hypocitraturia

In patients with mild to moderate hypocitraturia (urinary citrate > 150 mg/day) therapy should be initiated at 30 mEq/day (15 mEq two times/day or 10 mEq three times/day with meals or within 30 minutes after meals or bedtime snack). Twenty-four hour urinary citrate and/or urinary pH measurements should be used to determine the adequacy of the initial dosage and to evaluate the effectiveness of any dosage change. Doses of Urocit-K greater than 100 mEq/day have not been studied and should be avoided.

3 DOSAGE FORMS AND STRENGTHS

- 10 mEq tablets are uncoated, tan to yellowish in color, elliptical shaped, with 610 debossed on one side and MISSION on the other
- 15 mEq tablets are uncoated, tan to yellowish in color, modified rectangle shaped, with M15 debossed on one side and blank on the other

4 CONTRAINDICATIONS

Urocit®-K is contraindicated:

- In patients with hyperkalemia (or who have conditions pre-disposing them to hyperkalemia), as a further rise in serum potassium concentration may produce cardiac arrest. Such conditions include: chronic renal failure, uncontrolled diabetes mellitus, acute dehydration, strenuous physical exercise in unconditioned individuals, adrenal insufficiency, extensive tissue breakdown or the administration of a potassium-sparing agent (such as triamterene, spironolactone or amiloride).
- In patients in whom there is cause for arrest or delay in tablet passage through the gastrointestinal tract, such as those suffering from delayed gastric emptying, esophageal compression, intestinal obstruction or stricture, or those taking anticholinergic medication.
- In patients with peptic ulcer disease because of its ulcerogenic potential.
- In patients with active urinary tract infection (with either urea-splitting or other organisms, in association with either calcium or struvite stones). The ability of Urocit®-K to increase urinary citrate may be attenuated by bacterial enzymatic degradation of citrate. Moreover, the rise in urinary pH resulting from Urocit®-K therapy might promote further bacterial growth.
- In patients with renal insufficiency (glomerular filtration rate of less than 0.7 ml/kg/min), because of the danger of soft tissue calcification and increased risk for the development of hyperkalemia.

5 WARNINGS AND PRECAUTIONS

5.1 Hyperkalemia

In patients with impaired mechanisms for excreting potassium, Urocit-K administration can produce hyperkalemia and cardiac arrest. Potentially fatal hyperkalemia can develop rapidly and be asymptomatic. The use of Urocit-K in patients with chronic renal failure, or any other condition which impairs potassium excretion such as severe myocardial damage or heart failure, should be avoided. Closely monitor for signs of hyperkalemia with periodic blood tests and ECGs.

5.2 Gastrointestinal Lesions

Solid dosage forms of potassium chlorides have produced stenotic and/or ulcerative lesions of the small bowel and deaths. These lesions are caused by a high local concentration of potassium ions in the region of the dissolving tablets, which injured the bowel. In addition, perhaps because wax-matrix preparations are not enteric-coated and release some of their potassium content in the stomach, there have been reports of upper gastrointestinal bleeding associated with these products. The frequency of gastrointestinal lesions with wax-matrix potassium chloride products is estimated at one per 100,000 patient-years. Experience with Urocit-K is limited, but a similar frequency of gastrointestinal lesions should be anticipated.

If there is severe vomiting, abdominal pain or gastrointestinal bleeding, Urocit-K should be discontinued immediately and the possibility of bowel perforation or obstruction investigated.

6 ADVERSE REACTIONS

6.1 Postmarketing Experience

Some patients may develop minor gastrointestinal complaints during Urocit-K therapy, such as abdominal discomfort, vomiting, diarrhea, loose bowel movements or nausea. These symptoms are due to the irritation of the gastrointestinal tract, and may be alleviated by taking the dose with meals or snacks, or by reducing the dosage. Patients may find intact matrices in their feces.

7 DRUG INTERACTIONS

7.1 Potential Effects of Potassium Citrate on Other Drugs

Potassium-sparing Diuretics:Concomitant administration of Urocit-K and a potassium-sparing diuretic (such as triamterene, spironolactone or amiloride) should be avoided since the simultaneous administration of these agents can produce severe hyperkalemia.

7.2 Potential Effects of Other Drugs on Potassium Citrate

Drugs that slow gastrointestinal transit time:These agents (such as anticholinergics) can be expected to increase the gastrointestinal irritation produced by potassium salts.

7.3 Renin-Angiotensin-Aldosterone System Inhibitors

Drugs that inhibit the renin-angiotensin-aldosterone system (RAAS) including angiotensin converting enzyme (ACE) inhibitors, angiotensin receptor blockers (ARBs), spironolactone, eplerenone, or aliskiren produce potassium retention by inhibiting aldosterone production. Closely monitor potassium in patients receiving concomitant RAAS therapy.

7.4 Nonsteroidal Anti-Inflammatory Drugs (NSAIDs)

NSAIDs may produce potassium retention by reducing renal synthesis of prostagladin E and impairing the renin-angiotensin system. Closely monitor potassium in patients on concomitant NSAIDs.

8 USE IN SPECIFIC POPULATIONS

8.1 Pregnancy

Animal reproduction studies have not been conducted. It is also not known whether Urocit-K can cause fetal harm when administered to a pregnant woman or can affect reproduction capacity. Urocit-K should be given to a pregnant woman only if clearly needed.

8.3 Nursing Mothers

The normal potassium ion content of human milk is about 13 mEq/L. It is not known if Urocit-K has an effect on this content. Urocit-K should be given to a woman who is breastfeeding only if clearly needed.

8.4 Pediatric Use

Safety and effectiveness in children have not been established.

10 OVERDOSAGE

Treatment of Overdosage: The administration of potassium salts to persons without predisposing conditions for hyperkalemia rarely causes serious hyperkalemia at recommended dosages. It is important to recognize that hyperkalemia is usually asymptomatic and may be manifested only by an increased serum potassium concentration and characteristic electrocardiographic changes (peaking of T-wave, loss of P-wave, depression of S-T segment and prolongation of the QT interval). Late manifestations include muscle paralysis and cardiovascular collapse from cardiac arrest.

Treatment measures for hyperkalemia include the following:

1. Patients should be closely monitored for arrhythmias and electrolyte changes.

2. Elimination of medications containing potassium and of agents with potassium-sparing properties such as potassium-sparing diuretics, ARBs, ACE inhibitors, NSAIDs, certain nutritional supplements and many others.

3. Elimination of foods containing high levels of potassium such as almonds, apricots, bananas, beans (lima, pinto, white), cantaloupe, carrot juice (canned), figs, grapefruit juice, halibut, milk, oat bran, potato (with skin), salmon, spinach, tuna and many others.

4. Intravenous calcium gluconate if the patient is at no risk or low risk of developing digitalis toxicity.

5. Intravenous administration of 300-500 mL/hr of 10% dextrose solution containing 10-20 units of crystalline insulin per 1,000 mL.
6. Correction of acidosis, if present, with intravenous sodium bicarbonate.

7. Hemodialysis or peritoneal dialysis.
8. Exchange resins may be used. However, this measure alone is not sufficient for the acute treatment of hyperkalemia.

Lowering potassium levels too rapidly in patients taking digitalis can produce digitalis toxicity.

11 DESCRIPTION

Urocit-K is a citrate salt of potassium. Its empirical formula is K3C6H507 • H20, and it has the following chemical structure:

Urocit-K yellowish to tan, oral wax-matrix tablets, contain 5 mEq (540 mg) potassium citrate, 10 mEq (1080 mg) potassium citrate and 15 mEq (1620 mg) potassium citrate each. Inactive ingredients include carnauba wax and magnesium stearate.

12 CLINICAL PHARMACOLOGY

When Urocit-K is given orally, the metabolism of absorbed citrate produces an alkaline load. The induced alkaline load in turn increases urinary pH and raises urinary citrate by augmenting citrate clearance without measurably altering ultrafilterable serum citrate. Thus, Urocit-K therapy appears to increase urinary citrate principally by modifying the renal handling of citrate, rather than by increasing the filtered load of citrate. The increased filtered load of citrate may play some role, however, as in small comparisons of oral citrate and oral bicarbonate, citrate had a greater effect on urinary citrate.

In addition to raising urinary pH and citrate, Urocit-K increases urinary potassium by approximately the amount contained in the medication. In some patients, Urocit-K causes a transient reduction in urinary calcium.

The changes induced by Urocit-K produce urine that is less conducive to the crystallization of stone-forming salts (calcium oxalate, calcium phosphate and uric acid). Increased citrate in the urine, by complexing with calcium, decreases calcium ion activity and thus the saturation of calcium oxalate. Citrate also inhibits the spontaneous nucleation of calcium oxalate and calcium phosphate (brushite).

The increase in urinary pH also decreases calcium ion activity by increasing calcium complexation to dissociated anions. The rise in urinary pH also increases the ionization of uric acid to the more soluble urate ion.

Urocit-K therapy does not alter the urinary saturation of calcium phosphate, since the effect of increased citrate complexation of calcium is opposed by the rise in pH-dependent dissociation of phosphate. Calcium phosphate stones are more stable in alkaline urine.

In the setting of normal renal function, the rise in urinary citrate following a single dose begins by the first hour and lasts for 12 hours. With multiple doses the rise in citrate excretion reaches its peak by the third day and averts the normally wide circadian fluctuation in urinary citrate, thus maintaining urinary citrate at a higher, more constant level throughout the day. When the treatment is withdrawn, urinary citrate begins to decline toward the pre-treatment level on the first day.

The rise in citrate excretion is directly dependent on the Urocit-K dosage. Following long-term treatment, Urocit-K at a dosage of 60 mEq/day raises urinary citrate by approximately 400 mg/day and increases urinary pH by approximately 0.7 units.

In patients with severe renal tubular acidosis or chronic diarrheal syndrome where urinary citrate may be very low (<100 mg/day), Urocit-K may be relatively ineffective in raising urinary citrate. A higher dose of Urocit-K may therefore be required to produce a satisfactory citraturic response. In patients with renal tubular acidosis in whom urinary pH may be high, Urocit-K produces a relatively small rise in urinary pH.

12.1 Mechanism of Action

When Urocit®-K is given orally, the metabolism of absorbed citrate produces an alkaline load. The induced alkaline load in turn increases urinary pH and raises urinary citrate by augmenting citrate clearance without measurably altering ultrafilterable serum citrate. Thus, Urocit®-K therapy appears to increase urinary citrate principally by modifying the renal handling of citrate, rather than by increasing the filtered load of citrate. The increased filtered load of citrate may play some role, however, as in small comparisons of oral citrate and oral bicarbonate, citrate had a greater effect on urinary citrate.

In addition to raising urinary pH and citrate, Urocit®-K increases urinary potassium by approximately the amount contained in the medication. In some patients, Urocit®-K causes a transient reduction in urinary calcium.

The changes induced by Urocit®-K produce urine that is less conducive to the crystallization of stone-forming salts (calcium oxalate, calcium phosphate and uric acid). Increased citrate in the urine, by complexing with calcium, decreases calcium ion activity and thus the saturation of calcium oxalate. Citrate also inhibits the spontaneous nucleation of calcium oxalate and calcium phosphate (brushite).

The increase in urinary pH also decreases calcium ion activity by increasing calcium complexation to dissociated anions. The rise in urinary pH also increases the ionization of uric acid to the more soluble urate ion.

Urocit®-K therapy does not alter the urinary saturation of calcium phosphate, since the effect of increased citrate complexation of calcium is opposed by the rise in pH-dependent dissociation of phosphate. Calcium phosphate stones are more stable in alkaline urine.

In the setting of normal renal function, the rise in urinary citrate following a single dose begins by the first hour and lasts for 12 hours. With multiple doses the rise in citrate excretion reaches its peak by the third day and averts the normally wide circadian fluctuation in urinary citrate, thus maintaining urinary citrate at a higher, more constant level throughout the day. When the treatment is withdrawn, urinary citrate begins to decline toward the pre-treatment level on the first day.

The rise in citrate excretion is directly dependent on the Urocit®-K dosage. Following long-term treatment, Urocit®-K at a dosage of 60 mEq/day raises urinary citrate by approximately 400 mg/day and increases urinary pH by approximately 0.7 units.

In patients with severe renal tubular acidosis or chronic diarrheal syndrome where urinary citrate may be very low (<100 mg/day), Urocit®-K may be relatively ineffective in raising urinary citrate. A higher dose of Urocit®-K may therefore be required to produce a satisfactory citraturic response. In patients with renal tubular acidosis in whom urinary pH may be high, Urocit®-K produces a relatively small rise in urinary pH.

14 CLINICAL STUDIES

The pivotal Urocit-K trials were non-randomized and non-placebo controlled where dietary management may have changed coincidentally with pharmacological treatment. Therefore, the results as presented in the following sections may overstate the effectiveness of the product.

14.1 Renal Tubular Acidosis (RTA) with Calcium Stones

The effect of oral potassium citrate therapy in a non-randomized, non-placebo controlled clinical study of five men and four women with calcium oxalate/calcium phosphate nephrolithiasis and documented incomplete distal renal tubular acidosis was examined. The main inclusion criterion was a history of stone passage or surgical removal of stones during the 3 years prior to initiation of potassium citrate therapy. All patients began alkali treatment with 60-80 mEq potassium citrate daily in 3 or 4 divided doses. Throughout treatment, patients were instructed to stay on a sodium restricted diet (100 mEq/day) and to reduce oxalate intake (limited intake of nuts, dark roughage, chocolate and tea). A moderate calcium restriction (400-800 mg/day) was imposed on patients with hypercalciuria.

X-rays of the urinary tract, available in all patients, were reviewed carefully to determine presence of pre-existing stones, appearance of new stones, or change in the number of stones.

Potassium citrate therapy was associated with inhibition of new stone formation in patients with distal tubular acidosis. Three of the nine patients continued to pass stones during the on-treatment phase. While it is likely that these patients passed pre-existing stones during therapy, the most conservative assumption is that the passed stones were newly formed. Using this assumption, the stone-passage remission rate was 67%. All patients had a reduced stone formation rate. Over the first 2 years of treatment, the on-treatment stone formation rate was reduced from 13±27 to 1±2 per year.

14.2 Hypocitraturic Calcium Oxalate Nephrolithiasis of any Etiology

Eighty-nine patients with hypocitraturic calcium nephrolithiasis or uric acid lithiasis with or without calcium nephrolithiasis participated in this non-randomized, non-placebo controlled clinical study. Four groups of patients were treated with potassium citrate: Group 1 was comprised of 19 patients, 10 with renal tubular acidosis and 9 with chronic diarrheal syndrome, Group 2 was comprised of 37 patients, 5 with uric acid stones alone, 6 with uric acid lithiasis and calcium stones, 3 with type 1 absorptive hypercalciuria, 9 with type 2 absorptive hypercalciuria and 14 with hypocitraturia. Group 3 was comprised of 15 patients with history of relapse on other therapy and Group 4 was comprised of 18 patients, 9 with type 1 absorptive hypercalciuria and calcium stones, 1 with type 2 absorptive hypercalciuria and calcium stones, 2 with hyperuricosuric calcium oxalate nephrolithiasis, 4 with uric acid lithiasis accompanied by calcium stones and 2 with hypocitraturia and hyperuricemia accompanied by calcium stones. The dose of potassium citrate ranged from 30 to 100 mEq per day, and usually was 20 mEq administered orally 3 times daily. Patients were followed in an outpatient setting every 4 months during treatment and were studied over a period from 1 to 4.33 years. A three-year retrospective pre-study history for stone passage or removal was obtained and corroborated by medical records. Concomitant therapy (with thiazide or allopurinol) was allowed if patients had hypercalciuria, hyperuricosuria or hyperuricemia. Group 2 was treated with potassium citrate alone.

In all groups, treatment that included potassium citrate was associated with a sustained increase in urinary citrate excretion from subnormal values to normal values (400 to 700 mg/day), and a sustained increase in urinary pH from 5.6-6.0 to approximately 6.5. The stone formation rate was reduced in all groups as shown in Table 1.

Table 1. Effect of Urocit-K In Patients With Calcium Oxalate Nephrolithiasis.

*Remission defined as “the percentage of patients remaining free of newly formed stones during treatment”.

14.3 Uric Acid Lithiasis with or without Calcium Stones

A long-term non-randomized, non-placebo controlled clinical trial with eighteen adult patients with uric acid lithiasis participated in the study. Six patients formed only uric acid stones, and the remaining 12 patients formed mixed stones containing both uric acid and calcium salts or formed both uric acid stones (without calcium salts) and calcium stones (without uric acid) on separate occasions.

Eleven of the 18 patients received potassium citrate alone. Six of the 7 other patients also received allopurinol for hyperuricemia with gouty arthritis, symptomatic hyperuricemia, or hyperuricosuria. One patient also received hydrochlorothiazide because of unclassified hypercalciuria. The main inclusion criterion was a history of stone passage or surgical removal of stones during the 3 years prior to initiation of potassium citrate therapy. All patients received potassium citrate at a dosage of 30-80 mEq/day in three-to-four divided doses and were followed every four months for up to 5 years.

While on potassium citrate treatment, urinary pH rose significantly from a low value of 5.3 ± 0.3 to within normal limits (6.2 to 6.5). Urinary citrate which was low before treatment rose to the high normal range and only one stone was formed in the entire group of 18 patients.

16 HOW SUPPLIED/STORAGE AND HANDLING

Urocit-K 10 mEq tablets are uncoated, tan to yellowish in color, elliptical
shaped, with 610 debossed on one side and MISSION on the other, supplied
in bottles as:
NDC 0178-0610-01 Bottle of 100
Urocit-K 15 mEq tablets are uncoated, tan to yellowish in color,
modified rectangle shaped, with M15 debossed on one side and blank on
the other, supplied in bottles as:
NDC 0178-0615-01 Bottle of 100

Storage: Store in a tight container.

17 PATIENT COUNSELING INFORMATION

17.1 Administration of Drug

Tell patients to take each dose without crushing, chewing or sucking
the tablet.
Tell patients to take this medicine only as directed. This is especially
important if the patient is also taking both diuretics and digitalis
preparations.
Tell patients to check with the doctor if there is trouble swallowing
tablets or if the tablet seems to stick in the throat.
Tell patients to check with the doctor at once if tarry stools or other
evidence of gastrointestinal bleeding is noticed.
Tell patients that their doctor will perform regular blood tests and
electrocardiograms to ensure safety.

L061001R0625

PRINCIPAL DISPLAY PANEL - 10 mEq Bottle Label

NDC0178-0610-01

UROCIT®-K 10 mEq (Potassium Citrate)Extended-release tablet

10 mEq (1080 mg) per tablet

Rx only

100 Tablets

Mission Pharmacal Company, San Antonio, TX USA 78230

URK537R0725

PRINCIPAL DISPLAY PANEL - 15 mEq Bottle Label

NDC0178-0615-01

UROCIT®-K 15 mEq (Potassium Citrate)Extended-release tablet

15 mEq (1620 mg) per tablet

Rx only

100 Tablets

Mission Pharmacal Company, San Antonio, TX USA 78230

URK537R0725

PRINCIPAL DISPLAY PANEL - 5 mEq Bottle Label

NDC0178-0600-01

UROCIT ®-K 10 mEq (Potassium Citrate)Extended-release tablet

5 mEq (540 mg) per tablet

Rx only

100 Tablets

Mission Pharmacal Company, San Antonio, TX USA 78230 1355